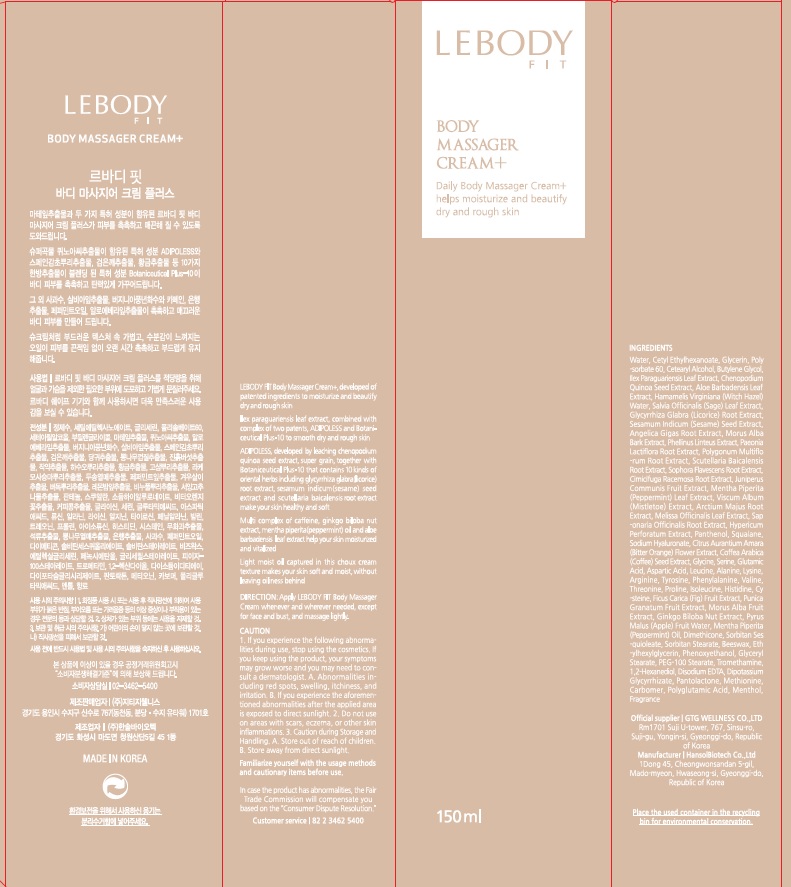 DRUG LABEL: LEBODY FIT BODY MASSAGER
NDC: 71080-0007 | Form: CREAM
Manufacturer: GTG Wellness Co., Ltd.
Category: otc | Type: HUMAN OTC DRUG LABEL
Date: 20181210

ACTIVE INGREDIENTS: ILEX PARAGUARIENSIS LEAF 3.0 g/150 mL
INACTIVE INGREDIENTS: Water; Cetyl Ethylhexanoate

ACTIVE INGREDIENT

Active ingredients: ILEX PARAGUARIENSIS LEAF EXTRACT 2.0%

INACTIVE INGREDIENT

Inactive ingredients:

Water, Cetyl Ethylhexanoate, Glycerin, Polysorbate 60, Cetearyl Alcohol, Butylene Glycol, Ilex Paraguariensis Leaf Extract, Chenopodium Quinoa Seed Extract, Aloe Barbadensis Leaf Extract, Hamamelis Virginiana (Witch Hazel) Water, Salvia Officinalis (Sage) Leaf Extract, Glycyrrhiza Glabra (Licorice) Root Extract, Sesamum Indicum (Sesame) Seed Extract, Angelica Gigas Root Extract, Morus Alba Bark Extract, Phellinus Linteus Extract, Paeonia Lactiflora Root Extract, Polygonum Multiflorum Root Extract, Scutellaria Baicalensis Root Extract, Sophora Flavescens Root Extract, Cimicifuga Racemosa Root Extract, Juniperus Communis Fruit Extract, Mentha Piperita (Peppermint) Leaf Extract, Viscum Album (Mistletoe) Extract, Arctium Majus Root Extract, Melissa Officinalis Leaf Extract, Saponaria Officinalis Root Extract, Hypericum Perforatum Extract, Panthenol, Squalane, Sodium Hyaluronate, Citrus Aurantium Amara (Bitter Orange) FlowerExtract, Coffea Arabica (Coffee) Seed Extract, Glycine, Serine, Glutamic Acid, Aspartic Acid, Leucine, Alanine, Lysine, Arginine, Tyrosine, Phenylalanine, Valine, Threonine, Proline, Isoleucine, Histidine, Cysteine, Ficus Carica (Fig) Fruit Extract, Punica Granatum Fruit Extract, Morus Alba Fruit Extract, Ginkgo Biloba Nut Extract, Pyrus Malus (Apple) Fruit Water, Mentha Piperita (Peppermint) Oil, Dimethicone, Sorbitan Sesquioleate, Sorbitan Stearate, Beeswax, Ethylhexylglycerin, Phenoxyethanol, Glyceryl Stearate, PEG-100 Stearate, Tromethamine, 1,2-Hexanediol, Disodium EDTA, Dipotassium Glycyrrhizate, Pantolactone, Methionine, Carbomer, Polyglutamic Acid, Menthol, Fragrance

PURPOSE

Purpose: Skin Conditioning

WARNINGS

Caution:

1. If you experience the following abnormalities during use, stop using the cosmetics. If you keep using the product, your symptoms may grow worse and you may need to consult a dermatologist.
A. Abnormalities including red spots, swelling, itchiness, and irritation.
B. If you experience the aforementioned abnormalities after the applied area is exposed to direct sunlight.
2. Do not use on area with scars, eczema, or other skin inflammations.
3. Caution during Storage and Handling.
A. Store out of reach of children.
B. Store away from direct sunlight.

KEEP OUT OF REACH OF CHILDREN

Store out of reach of children.

Uses

It provides nutrition and moisture to your skin effectively.

Directions

Apply LEBODY FIT Body massager Cream + whenever needed, except for face and bust, and massage lightly.